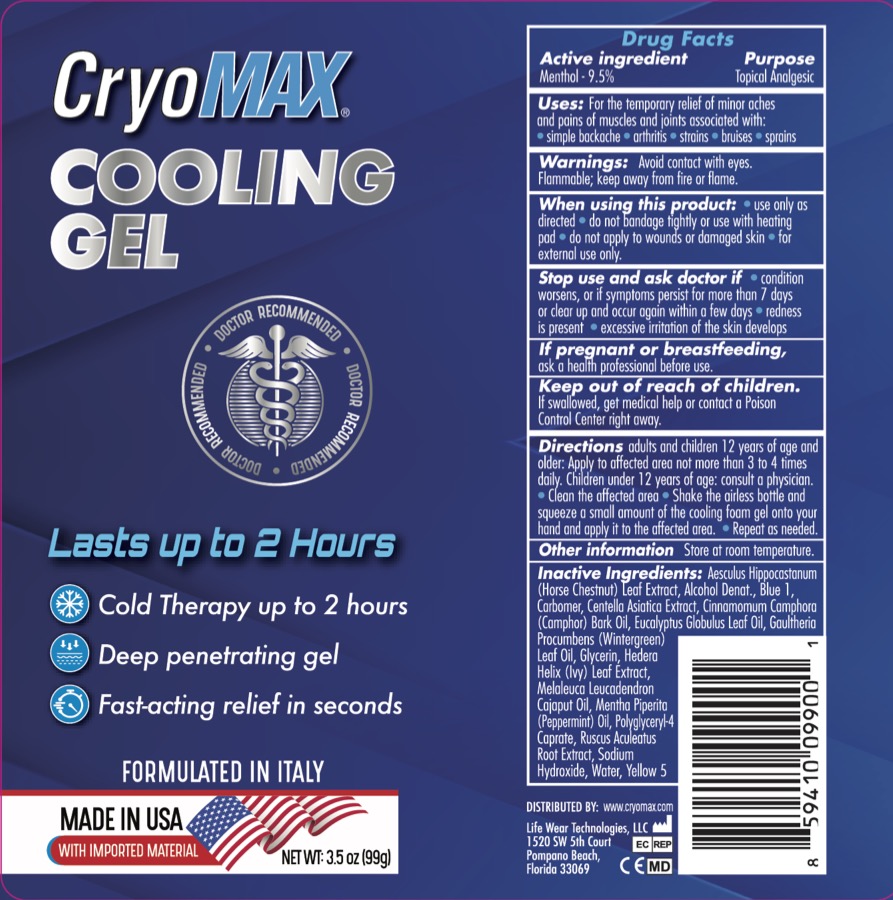 DRUG LABEL: Cryomax Cooling
NDC: 71207-461 | Form: GEL
Manufacturer: LIFE WEAR TECHNOLOGIES
Category: otc | Type: HUMAN OTC DRUG LABEL
Date: 20231113

ACTIVE INGREDIENTS: MENTHOL, (+)- 9.5 g/100 g
INACTIVE INGREDIENTS: HORSE CHESTNUT; ALCOHOL; FD&C BLUE NO. 1; CARBOMER 940; CENTELLA ASIATICA LEAF; CAMPHOR OIL; EUCALYPTUS OIL; METHYL SALICYLATE; GLYCERIN; WATER; HEDERA HELIX LEAF; MELALEUCA CAJUPUTI LEAF OIL; POLYGLYCERYL-4 CAPRATE; RUSCUS ACULEATUS ROOT; SODIUM HYDROXIDE; FD&C YELLOW NO. 5; PEPPERMINT OIL

Cryomax Cooling Gel

ACTIVE INGREDIENT

Menthol 9.5%

PURPOSE

Topical Analgesic

INDICATIONS AND USAGE

For the temporary relief of minor aches and pains of muscles and joints associated with

- simple backache
- arthritis
- strains
- bruises
- sprains

WARNINGS

For external use only.

When using this product avoid contact with eyes. Use only as directed. Do not bandage tightly or use with heating pad. Do not apply to wounds or damaged skin.

Flammable: keep away from fire or flame.

Stop use and ask a doctor if condition worsens or symptoms persist for more than 7 days or clear up and occur again within a few days, redness is present, excessive irritation of the skin develops.

KEEP OUT OF REACH OF CHILDREN

If swallowed, get medical help or contact a Poison Control Center right away.

DOSAGE AND ADMINISTRATION

- adults and children 12 years of age and older, apply to affected area not more than 3 to 4 times daily. Children under 12 years of age: consult a physician. Clean the affected area. Shake the airless bottle and squeeze a small amount of the cooling foam gel onto hand and apply it to the affected area. Repeat as necessary.

INACTIVE INGREDIENT

Aesculus Hippocastanum (Horse Chestnut) Leaf Extract, Alcohol Denat., Blue 1, Carbomer, Centella Asiatica Extract, Cinnamomum (Camphor) Bark Oil, Eucalyptus Globulus Leaf Oil, Gaultheria Procumbens (Wintergreen) Leaf Oil, Glycerin, Hedera Helix (Ivy) Leaf Extract, Melaleuca Leucadendron Cajoput Oil, Mentha Piperita (Peppermint) Oil, Polyglyceeryl-4 Caprate, Ruscus Aculeatus Root Extract, Sodium Hydroxide, Water, Yellow 5

PREGNANCY OR BREAST FEEDING

Ask a health professional before use.